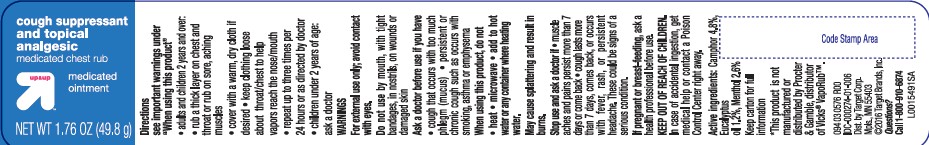 DRUG LABEL: cough suppressant and topical analgesic
NDC: 11673-667 | Form: OINTMENT
Manufacturer: Target Corporation
Category: otc | Type: HUMAN OTC DRUG LABEL
Date: 20260218

ACTIVE INGREDIENTS: CAMPHOR (SYNTHETIC) 48 mg/1 g; EUCALYPTUS OIL 12 mg/1 g; MENTHOL 26 mg/1 g
INACTIVE INGREDIENTS: CEDAR LEAF OIL; NUTMEG OIL; PETROLATUM; TURPENTINE; THYMOL

Up & Up 248.001/248AI
Medicated Chest Rub

Active Ingredients

Camphor 4.8%

Eucalyptus oil 1.2%

Menthol 2.6%

Purpose

Cough suppressant & topical analgesic

Uses

- on chest and throat, temporarily relieves cough due to common cold
- on muscles and joints, temporarily relieves minor aches and pains

Warnings

For external use only; avoid contact with eyes

Do not use

- by mouth
- with tight bandages
- in nostrils
- on wounds or damaged skin

Ask a doctor before us if you have

- cough that occurs with too much phlegm (mucus)
- persistent or chronic cough such as occurs with smoking, asthma or emphysema

When using this product, do not

- heat
- microwave
- add to hot water or any container where heating water. May cause splattering and result in burns.

Stop use and ask a doctor if

- muscle aches and pains persist more than 7 days or come back
- cough lasts more than 7 days, comes back, or occurs with fever, rash, or persisten headache. These could be signs of a serious condition.

If pregnant or breast-feeding

ask a health professional before use

Keep out of reach of children.

In case of accidental ingestion, get medical help or contact a Poison Control center right away.

Directions

see important warnings under "When using this product"

- adults & children 2 yrs & over:
- rub a thick layer on chest and throat or rub on sore aching muscles
- cover with a warm dry cloth if desired
- keep clothing loose about thorat/chest to help vapors reach the nose/mouth
- repeat up to three times per 24 hours or directed by doctor
- children under 2 years of age: ask a doctor

Other information

- store at room temperature

Inactive ingredients

cedarleaf oil, nutmeg oil, special petrolatum, spirits of turpentine, thymol

Questions?

1-800-910-6874

adverse reactions section

FAILURE TO FOLLOW THESE WARNINGS COULD RESULT IN SERIOUS CONSEQUENCES

*This product is not manufactured or distributed by Procter & Gamble, distributor of Vicks®VapoRub®

Dist. By Target Corp.

Mpls., MN 55403

Principal display panel

cough supressant and topical analgesic

medicated chest rub

medicated ointment

up & up™

NET WT 1.76 OZ (49.8 g)